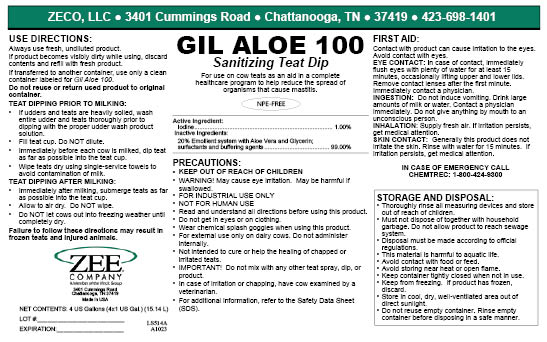 DRUG LABEL: Gil Aloe 100
NDC: 86161-006 | Form: LIQUID
Manufacturer: ZECO, LLC
Category: animal | Type: OTC ANIMAL DRUG LABEL
Date: 20240124

ACTIVE INGREDIENTS: iodine 10 g/1 L
INACTIVE INGREDIENTS: C12-16 PARETH-5; ANHYDROUS CITRIC ACID; GLYCERIN; ALOE VERA LEAF

Gil Aloe 100

PURPOSE

Sanitizing Teat Dip

For use on cow teats as an aid in a complete healthcare program to help reduce the spread of organisms that cause mastitis.

Acive Ingredient:

Iodine ........................................................1.00%

PRECAUTIONS:

- KEEP OUT OF REACH OF CHILDREN
- WARNING: May cause eye irritation. May be harmful if swallowed.
- FOR INDUSTRIAL USE ONLY
- NOT FOR HUMAN USE
- Read and understand all directions before using this product.
- Do not get in eyes or on clothing.
- Wear chemical splash goggles when using this product.
- For external use only on dairy cows. Do not administer internally.
- Not intended to cure or help the healing of chapped or irritated teats.
- IMPORTANT: Do not mix with any other teat spray, dip, or product.
- In case of irritation or chapping, have cow examined by a veterinarian.
- For additional information refer to the Safety Data Sheet (SDS).

DOSAGE AND ADMINISTRATION

USE DIRECTIONS:

Always use fresh, undiluted product.

If product becomes visibly dirty while using, discard contents and refill with fresh product.

If transferred to another container: use only a clean container labeled for Gil Aloe 100.

Do not reuse or return used product to original container.

TEAT DIPPING PRIOR TO MILKING:

- If udders and teats are heavily soiled, wash entire udder and teats thoroughly prior to dipping with the proper udder wash product solution.
- Fill teat cup. Do NOT dilute.
- Immediately before each cow is milked, dip teat as far as possible into the teat cup.
- Wipe teats dry using single-service towels to avoid contamination of milk.

TEAT DIPPING AFTER MILKING:

- Immediately after milking, submerge teats as far as possible into the teat cup.
- Allow to air dry. Do NOT wipe.
- Do NOT let cows out into freezing weather until completely dry.

Failure to follow these directions may result in frozen teats and injured animals.

PACKAGE LABEL

Add image transcription here...